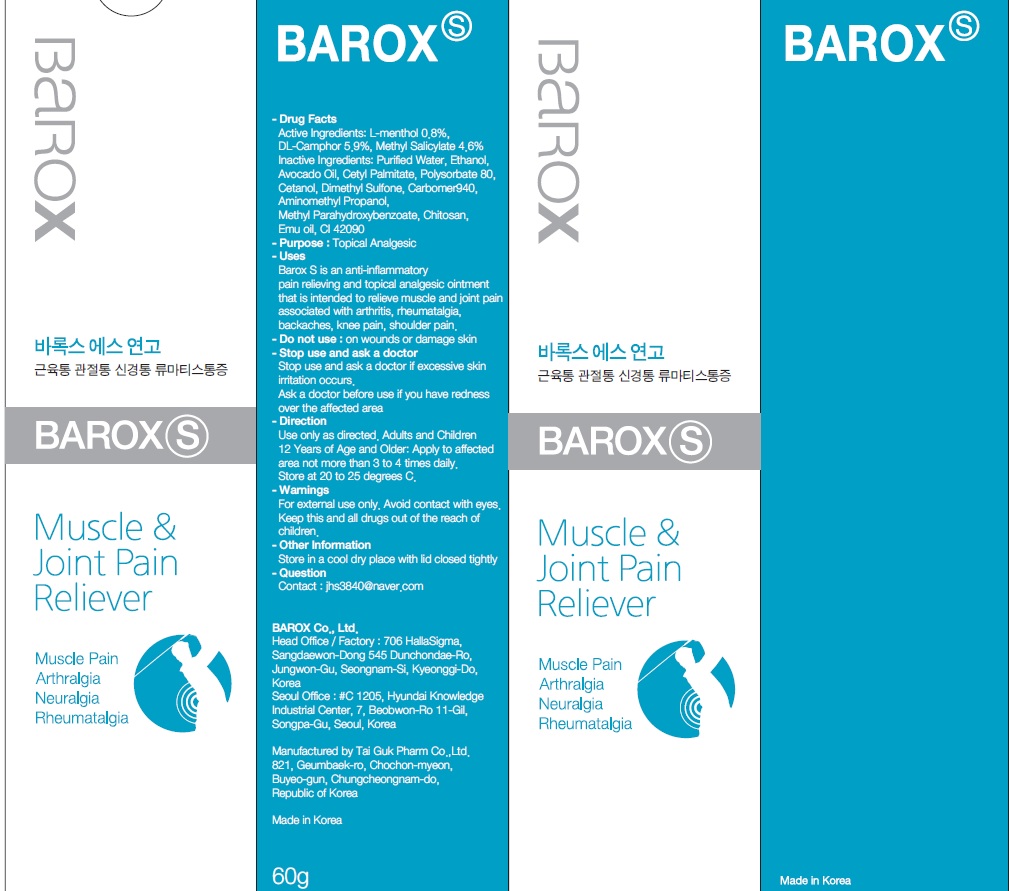 DRUG LABEL: BAROX S 60g
NDC: 55692-210 | Form: GEL
Manufacturer: Barox Co., Ltd.
Category: otc | Type: HUMAN OTC DRUG LABEL
Date: 20180914

ACTIVE INGREDIENTS: CAMPHOR (SYNTHETIC) 3.54 g/60 g; METHYL SALICYLATE 2.76 g/60 g; MENTHOL 0.48 g/60 g
INACTIVE INGREDIENTS: Water; AVOCADO OIL

ACTIVE INGREDIENT

Active ingredients: L-menthol 0.8%, DL-Camphor 5.9%, Methyl Salicylate 4.6%

INACTIVE INGREDIENT

Inactive Ingredients: Purified Water, Ethanol, Avocado Oil, CetylPalmitate, Polysorbate 80, Cetanol, Dimethyl Sulfone, Carbomer940, Aminomethyl Propanol, Methyl Parahydroxybenzoate, Chitosan, Emu oil, CI 42090

PURPOSE

Purpose: Topical Analgesic

WARNINGS

For external use only. Avoid contact with eyes. Keep this and all drugs out of the reach of children.

KEEP OUT OF REACH OF CHILDREN

Keep this and all drugs out of the reach of children.

Uses

Barox S is an anti-inflammatory pain relieving and topical analgesic ointment that is intended to relieve muscle and joint pain associated with arthritis, rheumatalgia, backaches, knee pain, shoulder pain.

Direction

Use only as directed. Adults and Children 12 Years of Age and Older: Apply to affected area not more than 3 to 4 times daily.

QUESTIONS

www.barox.co.kr